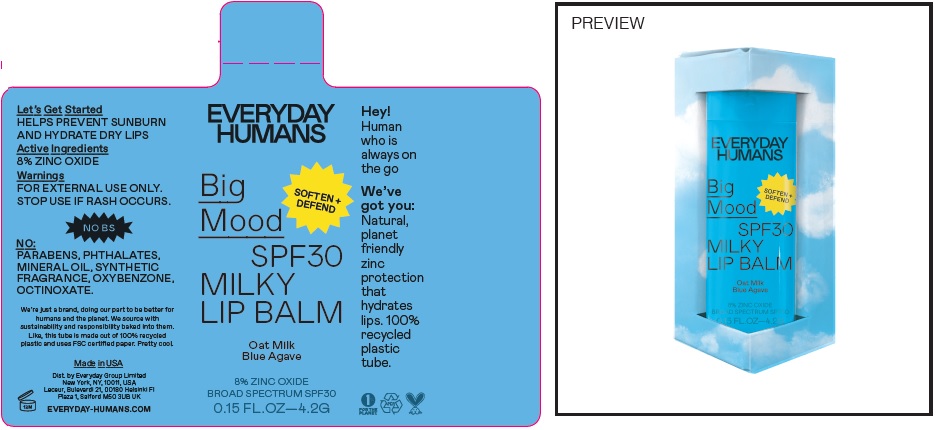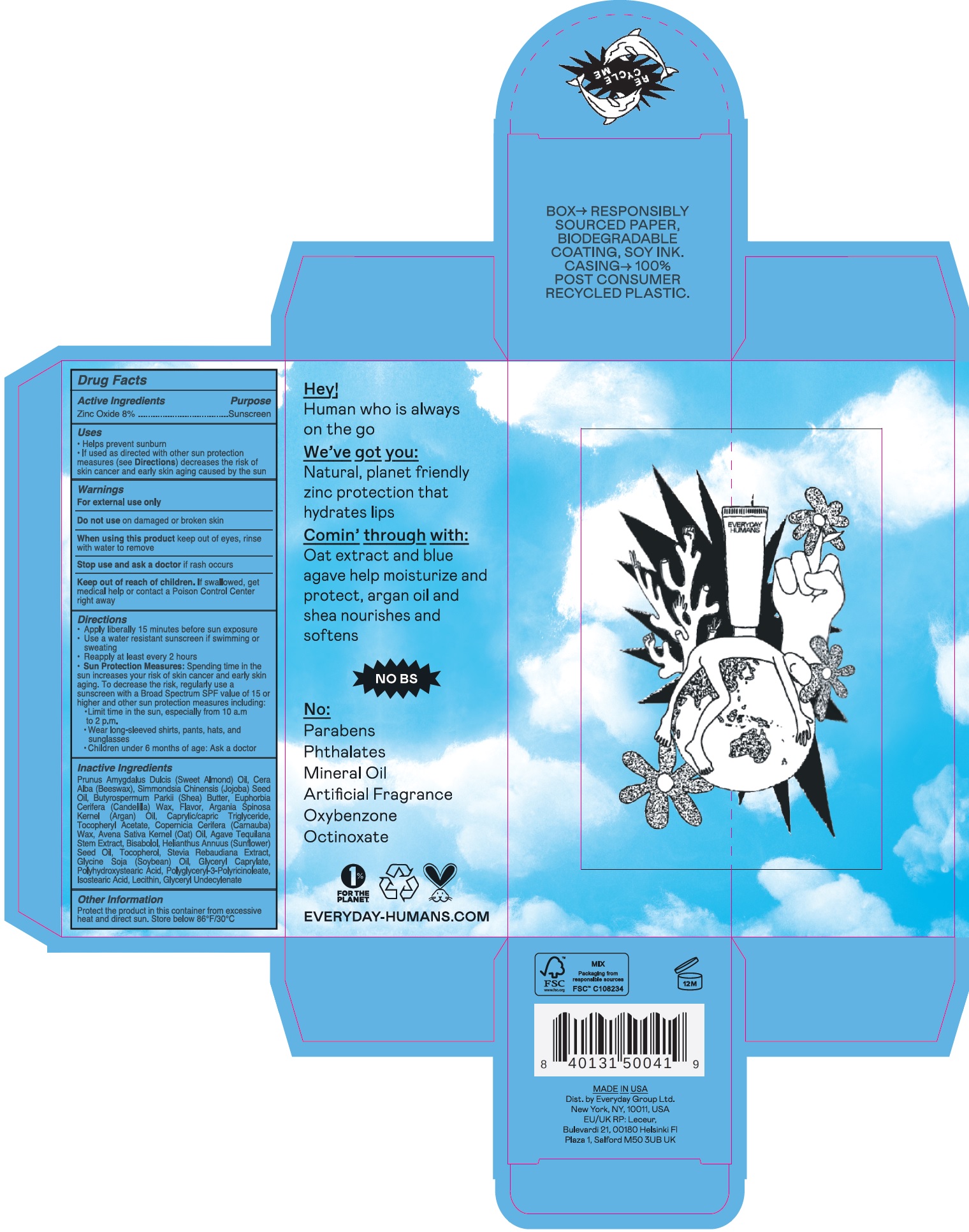 DRUG LABEL: Big Mood SPF 30 Milky Lip Balm
NDC: 72098-004 | Form: STICK
Manufacturer: Everyday Group Limited
Category: otc | Type: HUMAN OTC DRUG LABEL
Date: 20231109

ACTIVE INGREDIENTS: ZINC OXIDE 80 mg/1 g
INACTIVE INGREDIENTS: TRICAPRYLIN; ARGAN OIL; YELLOW WAX; ALMOND OIL; JOJOBA OIL; SHEA BUTTER; CANDELILLA WAX; METHYL SALICYLATE; MEDIUM-CHAIN TRIGLYCERIDES; .ALPHA.-TOCOPHEROL ACETATE; CARNAUBA WAX; OAT; LEVOMENOL; SUNFLOWER OIL; TOCOPHEROL; SOYBEAN OIL; GLYCERYL CAPRYLATE; POLYGLYCERYL-3 PENTARICINOLEATE; ISOSTEARIC ACID

Big Mood SPF 30 Milky Lip Balm

Active Ingredients

Zinc Oxide 8%

Purpose

Sunscreen

Uses

- Helps prevent sunburn
- If used as directed with other sun protection measures (see) decreases the risk of skin cancer and early skin aging caused by the sun Directions

Warnings

For external use only

Do not use

on damaged or broken skin

When using this product

keep out of eyes, rinse with water to remove

Stop use and ask a doctor

if rash occurs

Keep out of reach of children.

If swallowed, get medical help or contact a Poison Control Center right away

Directions

- Apply liberally 15 minutes before sun exposure
- Use a water resistant sunscreen if swimming or sweating
- Reapply at least every 2 hours
- Spending time in the sun increases your risk of skin cancer and early skin aging. To decrease the risk, regularly use a sunscreen with a Broad Spectrum SPF value of 15 or higher and other sun protection measures including: Sun Protection Measures:
- Limit time in the sun, especially from 10 a.m to 2 p.m.
- Wear long-sleeved shirts, pants, hats, and sunglasses
- Children under 6 months of age: Ask a doctor

Inactive Ingredients

Prunus Amygdalus Dulcis (Sweet Almond) Oil, Cera Alba (Beeswax), Simmondsia Chinensis (Jojoba) Seed Oil, Butyrospermum Parkii (Shea) Butter, Euphorbia Cerifera (Candelilla) Wax, Flavor, Argania Spinosa Kernal (Argan) Oil, Caprylic/capric Triglyceride, Tocopheryl Acetate, Copernicia Cerifera (Carnauba) Wax, Avena Sativa Kernel (Oat) Oil, Agave Tequilana Stem Extract, Bisabolol, Helianthus Annuus (Sunflower) Seed Oil, Tocopherol, Stevia Rebaudiana Extract, Glycine Soja (Soybean) Oil, Glyceryl Caprylate, Polyhydroxystearic Acid, Polyglyceryl-3-Polyricinoleate, Isostearic Acid, Lecithin, Glyceryl Undecylenta

Other Information

Protect the product in this container from excessive heat and direct sun. Store below 86°F/30°C